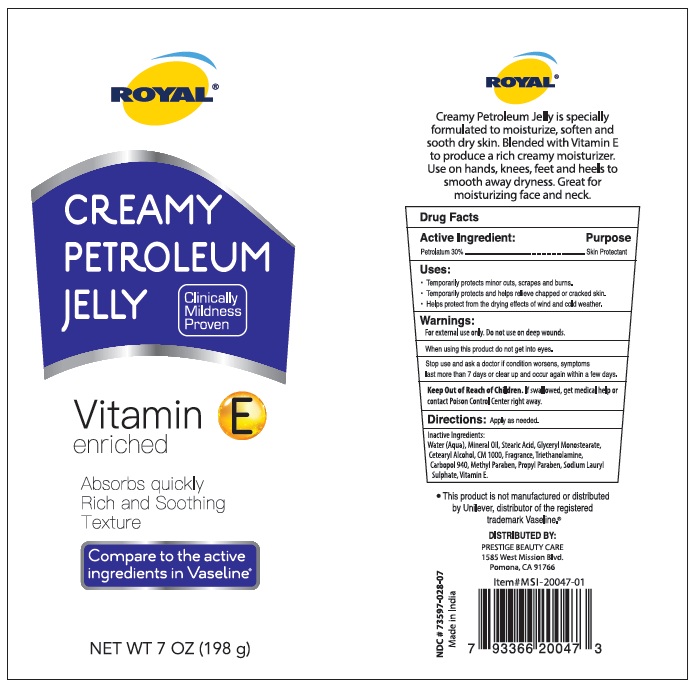 DRUG LABEL: ROYAL CREAMY PETROELUM
NDC: 85891-011 | Form: CREAM
Manufacturer: SPARROW LIFE CARE PRIVATE LIMITED
Category: otc | Type: HUMAN OTC DRUG LABEL
Date: 20251212

ACTIVE INGREDIENTS: PETROLATUM 30 g/100 g
INACTIVE INGREDIENTS: MINERAL OIL; METHYLPARABEN; WATER; .ALPHA.-TOCOPHEROL; STEARIC ACID; GLYCERYL MONOSTEARATE; PROPYLPARABEN; SODIUM LAURYL SULFATE; CARBOMER HOMOPOLYMER TYPE C (ALLYL PENTAERYTHRITOL CROSSLINKED); CETOSTEARYL ALCOHOL; CETETH-20; TROLAMINE

Active Ingredient Purpose

Petrolatum 30% Skin Protectant

Uses

- Temporarily protects minor cuts, scrapes, and burns.
- Temporarily protects and helps relieve chapped or cracked skin.
- Helps protect from the drying effects of wind and cold weather.

Warnings

- For external use only. Do not use on deep wounds.
- When using this product do not get into eyes.
- Stop use and ask a doctor if condition worsens, symptoms last more than 7 days, or clear up and occur again within a few days.
- Keep Out of Reach of Children. If swallowed, get medical help or contact a Poison Control Center right away.

Directions

Apply as needed.

Inactive ingredients

Water (Aqua), Mineral Oil, Stearic Acid, Glyceryl Monostearate, Cetearyl Alcohol, CM 1000, Fragrance, Triethanolamine, Carbopol 940, Methyl Paraben, Propyl Paraben, Sodium Lauryl Sulphate, Vitamin E.